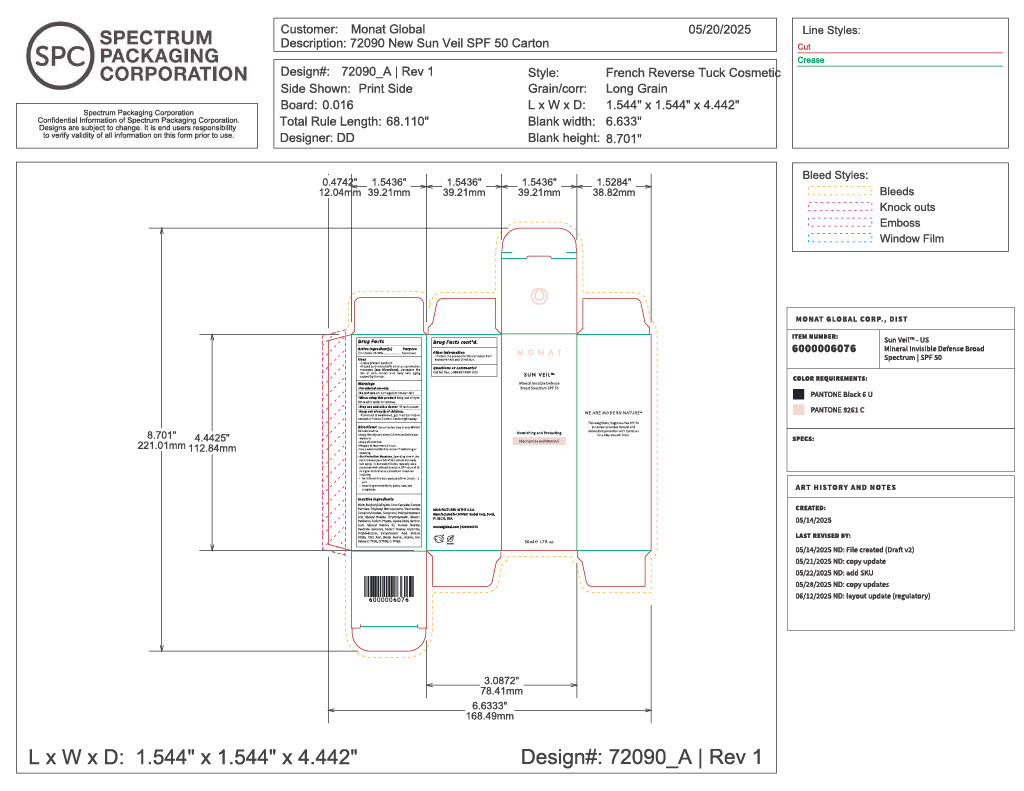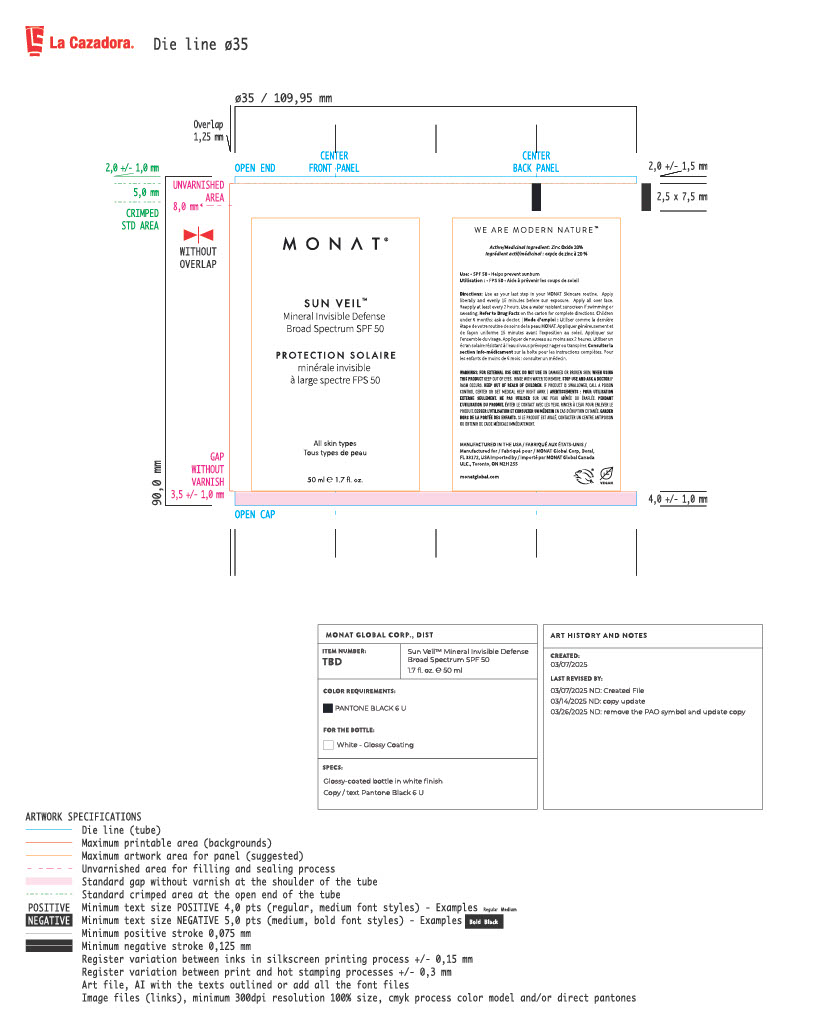 DRUG LABEL: Sun Veil Broad Spectrum SPF50
NDC: 78518-014 | Form: LOTION
Manufacturer: MONAT GLOBAL CORP
Category: otc | Type: HUMAN OTC DRUG LABEL
Date: 20251006

ACTIVE INGREDIENTS: ZINC OXIDE 20 mg/100 mg
INACTIVE INGREDIENTS: COCO-CAPRYLATE; OCTYLDODECANOL; POLYHYDROXYSTEARIC ACID (2300 MW); TRIHYDROXYSTEARIN; ALPHA-TOCOPHEROL ACETATE; WATER; SUCROSE PALMITATE; ETHYLHEXYL METHOXYCRYLENE; NIACINAMIDE; TOCOPHEROL; POTASSIUM HYDROLYZED JOJOBA ESTERS; GLYCERYL STEARATE; GLYCERIN; SODIUM PHYTATE; GLYCERYL STEARATE SE; SUCROSE STEARATE; SACCHARIDE ISOMERATE; SODIUM STEAROYL GLUTAMATE; DEHYDROACETIC ACID; SODIUM CITRATE; CITRIC ACID; CI 77492; CI 77499; ALCOHOL; CI 77491; PANTHENOL; BUTYLOCTYL SALICYLATE; BENZYL ALCOHOL; XANTHAN GUM

MONAT Sun Veil™ SPF 50

Active ingredient

Zinc Oxide 20.0%

Purpose

Sunscreen

Uses

- Helps prevent sunburn
- If used as directed with other sun protection measures (see Directions), decreases the risk of skin cancer and early skin aging caused by the sun.

WARNINGS

- For external use only

- Do not use on damaged or broker skin.

- When using this product keep out of eyes. Rinse with water to remove.

- Stop use and ask a doctor .
- if rash occurs.

- Keep out of reach of children.
- If product is swallowed, get medical help or contact a Poison Control Center right away.

Directions

Directions: Use as the last step in your MONAT skincare routine.

- Apply liberally and evenly 15 minutes before sun exposure
- Apply all over face
- Reapply at least every 2 hours
- Use a water-resistant sunscreen if swimming or sweating
- Sun Protection Measures. Spending time in the sun increases you risk od skin cancer and early skin aging. To decrease this risk, regularly use a sunscreen with Broad Spectrum SPF value of 15 or higheri and other sun protection measures including.
- limit time in the sun, especially form 10am-2pm
- wear long-sleeved shirts, pants, hats, and sunglasses

Inactive ingredients:

Water, Butyloctyl Salicylate, Coco-Caprylate, Sucrose Palmitate, Ethylhexyl Methoxycrylene, Niacinamide, Tocopheryl Acetate, Tocopherol, Polyhydroxystearic Acid, Glyceryl Stearate, Trihydroxystearin, Glycerin, Panthenol, Sodium Phytate, Jojoba Esters, Xanthan Gum, Glyceryl Stearate SE, Sucrose Stearate, Saccharide Isomerate, Sodium Stearoyl Glutamate, Octyldodecanol, Dehydroacetic Acid, Sodium Citrate, Citric Acid, Benzyl Alcohol, Alcohol, Iron Oxides (CI 77492), Iron Oxides (CI 77491), Iron Oxides (CI 77499).